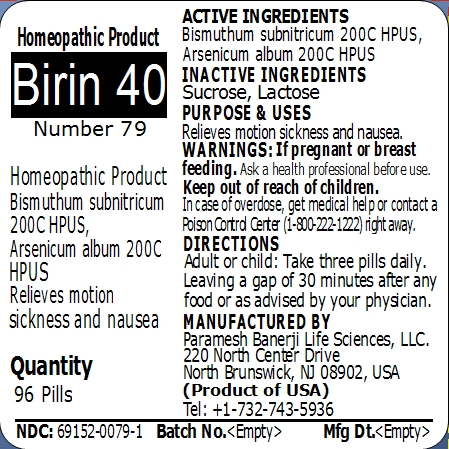 DRUG LABEL: Birin 40 (Number 79)
NDC: 69152-0079 | Form: PELLET
Manufacturer: Paramesh Banerji Life Sciences LLC
Category: homeopathic | Type: HUMAN OTC DRUG LABEL
Date: 20150209

ACTIVE INGREDIENTS: ARSENIC TRIOXIDE 200 [hp_C]/1 1; BISMUTH SUBNITRATE 200 [hp_C]/1 1
INACTIVE INGREDIENTS: SUCROSE; LACTOSE

Active Ingredients

Bismuthum subnitricum 200C HPUS, Arsenicum album 200C HPUS

Inactive Ingredients

Sucrose, Lactose

Purpose

Relieves motion sickness and nausea

Uses

Relieves motion sickness and nausea

Warnings

If pregnant or breast feeding ask a health professional before use.

Keep out of reach of children. In case of overdose, get medical help or contact a Poison Control Center (1-800-222-1222) right away.

Direction

Adult or child: Take three pills daily. Leaving a gap of 30 minutes after any food or as advised by your physician.

Manufactured by

Paramesh Banerji Life Sciences, LLC

220 North Center Drive

North Brunswick, NJ 08902, USA

Product of USA

Tel: +1-732-743-5936

Principal Display Panel

Homeopathic Product

Birin 40

Number 79

Homeopathic Product

Bismuthum subnitricum 200C HPUS, Arsenicum album 200C HPUS

Relieves motion sickness and nausea

Quantity

96 Pills